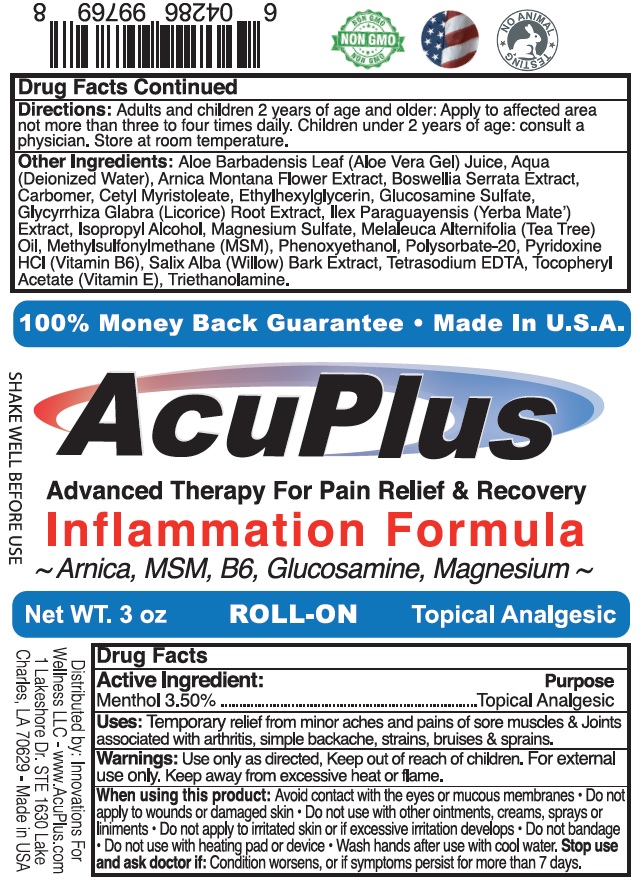 DRUG LABEL: AcuPlus Advanced Therapy for Pain and Recovery
NDC: 72037-136 | Form: SOLUTION
Manufacturer: INNOVATIONS FOR WELLNESS, LLC
Category: otc | Type: HUMAN OTC DRUG LABEL
Date: 20231105

ACTIVE INGREDIENTS: MENTHOL 35 mg/1 mL
INACTIVE INGREDIENTS: ALOE VERA LEAF; WATER; ARNICA MONTANA FLOWER; INDIAN FRANKINCENSE; CARBOXYPOLYMETHYLENE; CETYL MYRISTOLEATE; ETHYLHEXYLGLYCERIN; GLUCOSAMINE SULFATE; LICORICE; ILEX PARAGUARIENSIS WHOLE; ISOPROPYL ALCOHOL; MAGNESIUM SULFATE, UNSPECIFIED FORM; TEA TREE OIL; DIMETHYL SULFONE; PHENOXYETHANOL; POLYSORBATE 20; PYRIDOXINE HYDROCHLORIDE; SALIX ALBA BARK; EDETATE SODIUM; .ALPHA.-TOCOPHEROL ACETATE; TROLAMINE

AcuPlus Advanced Therapy for Pain and Recovery

Active Ingredient:

Menthol 3.50%

Purpose

Topical Analgesic

Uses:

Temporary relief from minor aches and pains of sore muscles & Joints associated with arthritis, simple backache, strains, bruises & sprains.

Warnings:

Use only as directed.

Keep out of reach of children

For external use only. Keep away from excessive heat or flame.

When using this product:

Avoid contact with the eyes or mucous membranes.

Do not apply

- to wounds or damaged skin.
- Do not use with other ointments, creams, sprays or liniments.
- Do not apply to irritated skin or if excessive irritation develops
- Do not bandage
- Do not use with heating pad or device
- Wash hands after use with cool water.

Stop use and ask doctor if:

Condition worsens, or if symptoms persist for more than 7 days.

Directions:

Adults and children 2 years of age and older: Apply to affected area not more than three to four times daily. Children under 2 years of age: consult a physician. Store at room temperature.

Other Ingredients:

Aloe Barbadensis Leaf (Aloe Vera Gel) Juice, Aqua (Deionized Water), Arnica Montana Flower Extract, Boswellia Serrata Extract, Carbomer, Cetyl Myristoleate, Ethylhexylglycerin, Glucosamine Sulfate, Glycyrrhiza Glabra (licorice) Root Extract, Ilex Paraguayensis (Yerba Mate') Extract, Isopropyl Alcohol, Magnesium Sulfate, Melaleuca Alternifolia (Tea Tree) Oil, Methylsulfonylmethane (MSM), Phenoxyethanol, Polysorbate-20, Pyridoxine HCl (Vitamin B6), Salix Alba (Willow) Bark Extract, Tetrasodium EDTA, Tocophyeryl Acetate (Vitamin E), Triethanolamine.